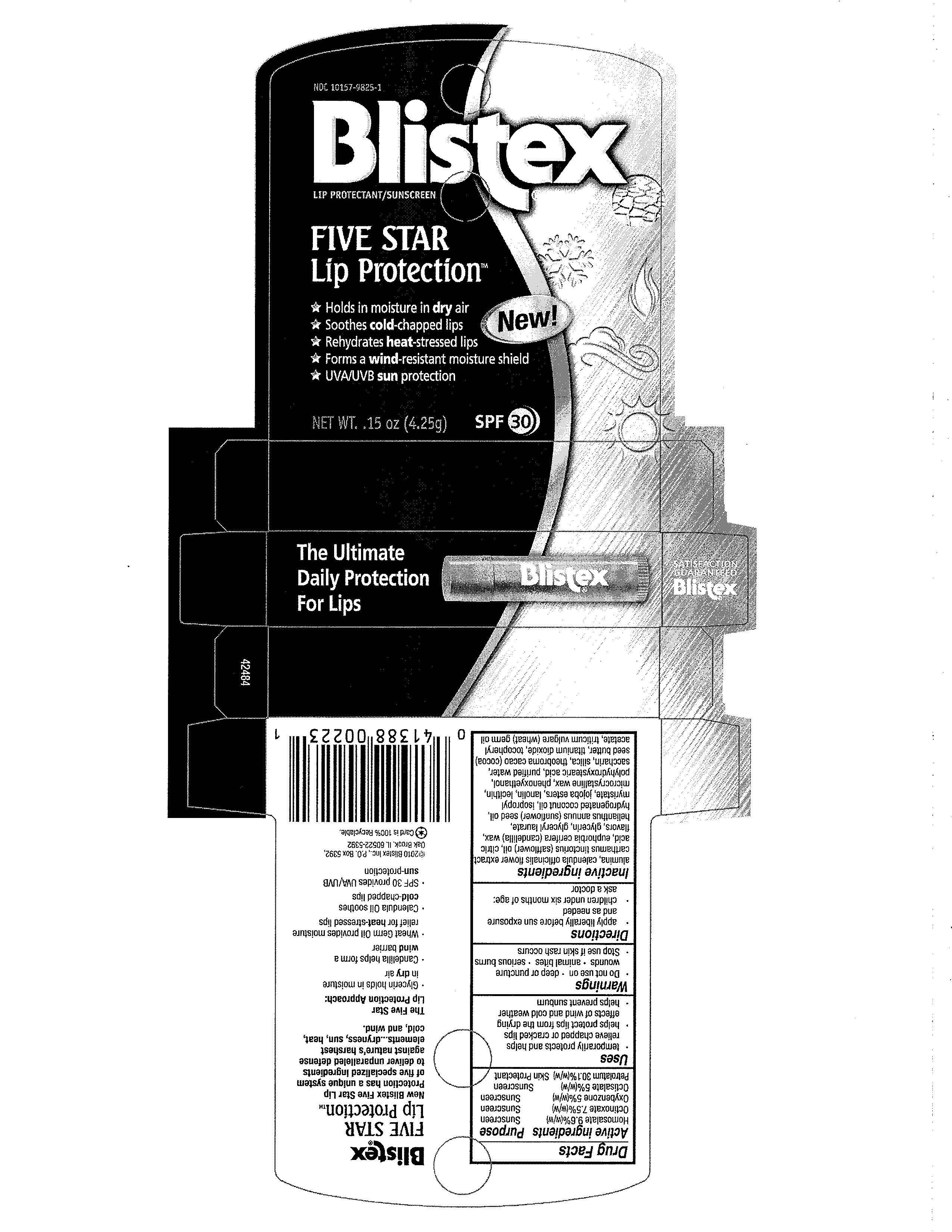 DRUG LABEL: Blistex 
NDC: 10157-9825 | Form: STICK
Manufacturer: Blistex Inc
Category: otc | Type: HUMAN OTC DRUG LABEL
Date: 20100108

ACTIVE INGREDIENTS: PETROLATUM	 30.1 g/1 1; HOMOSALATE 9.6 g/1 1; OCTISALATE 5.0 g/1 1; OCTINOXATE	 7.5 g/1 1; OXYBENZONE 5.0 g/1 1

DRUG FACTS

ACTIVE INGREDIENT

Petrolatum

Hemosalate

Octinoxate

Oxybenzone

Octisalate

PURPOSE

SKIN PROTECTANT/ SUNSCREEN

WHEN USING

- Temporarily protects and helps relieve chapped or cracked lips

- Helps protect lips from the drying effects of wind, cold weather

- Helps prevent sunburn

FOR EXTERNAL USE ONLY

- Do not use on * deep puncture wounds* animal bites* serious burns
- Stop use if skin rash occurs
- Adults and children 2 years of age and older: apply liberally to affected area not more than 3 to 4 times daily.
- Children under 2 years of age : consult a doctor.

PACKAGE LABEL

BLISTEX
FIVE STAR
LIP PROTECTION

- Holds in moisture in Dry air
- Soothes cold chapped lips
- Rehydrates heat stressed lips
- Forms a wind resistant moisture shield
- UVA/UVB sun protection

NET WT. .15oz. (4.25g) SPF